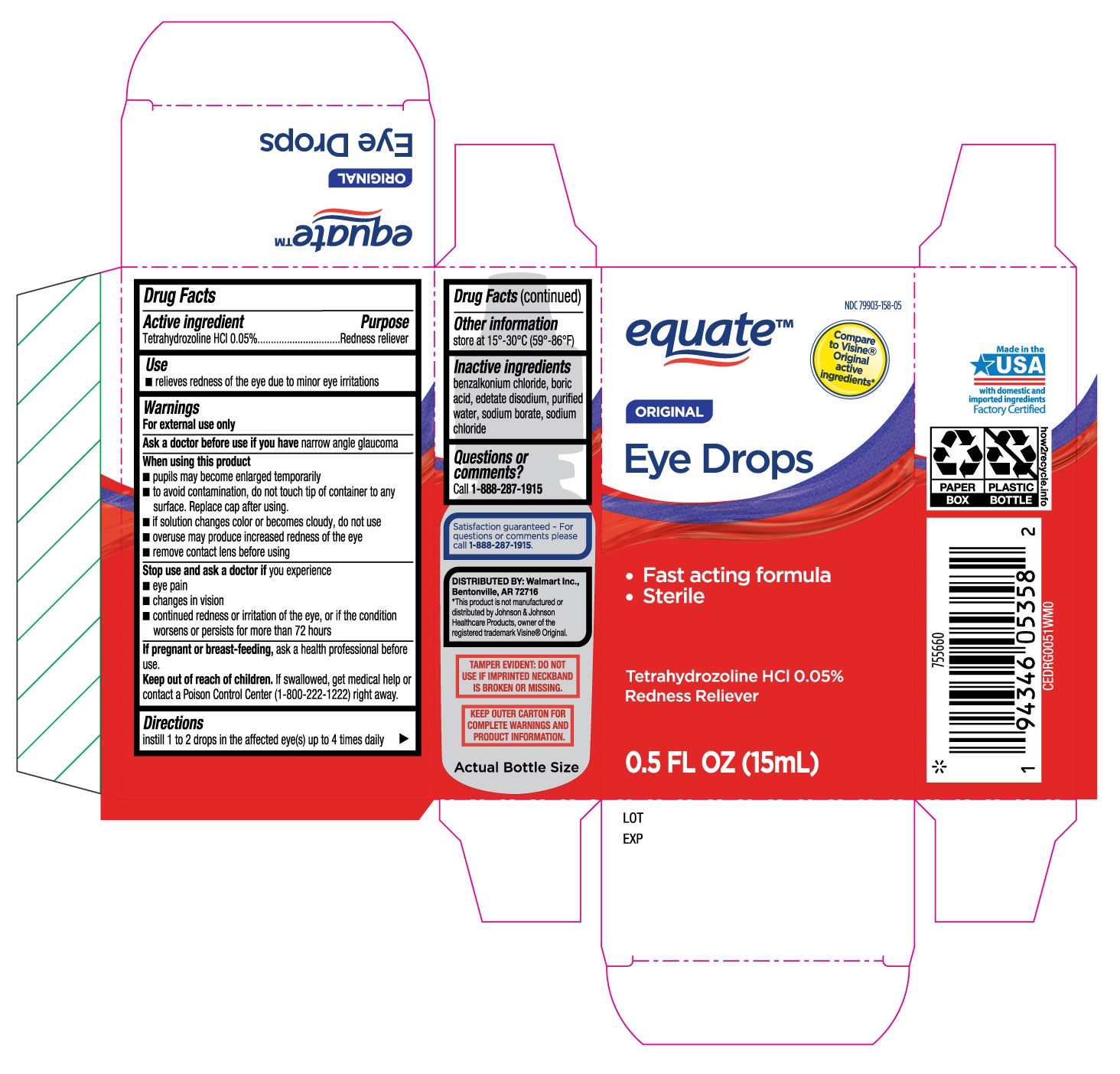 DRUG LABEL: Equate Original Eye Drops
NDC: 79903-158 | Form: SOLUTION/ DROPS
Manufacturer: Walmart, Inc.
Category: otc | Type: HUMAN OTC DRUG LABEL
Date: 20251230

ACTIVE INGREDIENTS: TETRAHYDROZOLINE HYDROCHLORIDE 0.05 g/100 mL
INACTIVE INGREDIENTS: BORIC ACID; EDETATE DISODIUM; WATER; SODIUM BORATE; BENZALKONIUM CHLORIDE; SODIUM CHLORIDE

Equate Original Eye Drops 15mL (PLD)

Active ingredient

Tetrahydrozoline HCl 0.05%

Purpose

Redness reliever

Use

- relieves redness of the eye due to minor eye irritations

Warnings

For external use only

Ask a doctor before use if you have

narrow angle glaucoma

When using this product

- pupils may become enlarged temporarily
- to avoid contamination, do not touch tip of container to any surface. Replace cap after using.
- if solution changes color or becomes cloudy, do not use
- overuse may produce increased redness of the eye
- remove contact lens before using

Stop use and ask a doctor if

you experience

- eye pain
- changes in vision
- continued redness or irritation of the eye, or if the condition worsens or persists for more than 72 hours

If pregnant or breast-feeding,

ask a health professional before use.

Keep out of reach of children.

If swallowed, get medical help or contact a Poison Control Center (1-800-222-1222) right away.

Directions

instill 1 to 2 drops in the affected eye(s) up to 4 times daily

Other information

store at 15°-30°C (59°-86°F)

Inactive ingredients

benzalkonium chloride, boric acid, edetate disodium, purified water, sodium borate, sodium chloride

Questions or comments?

Call 1-888-287-1915